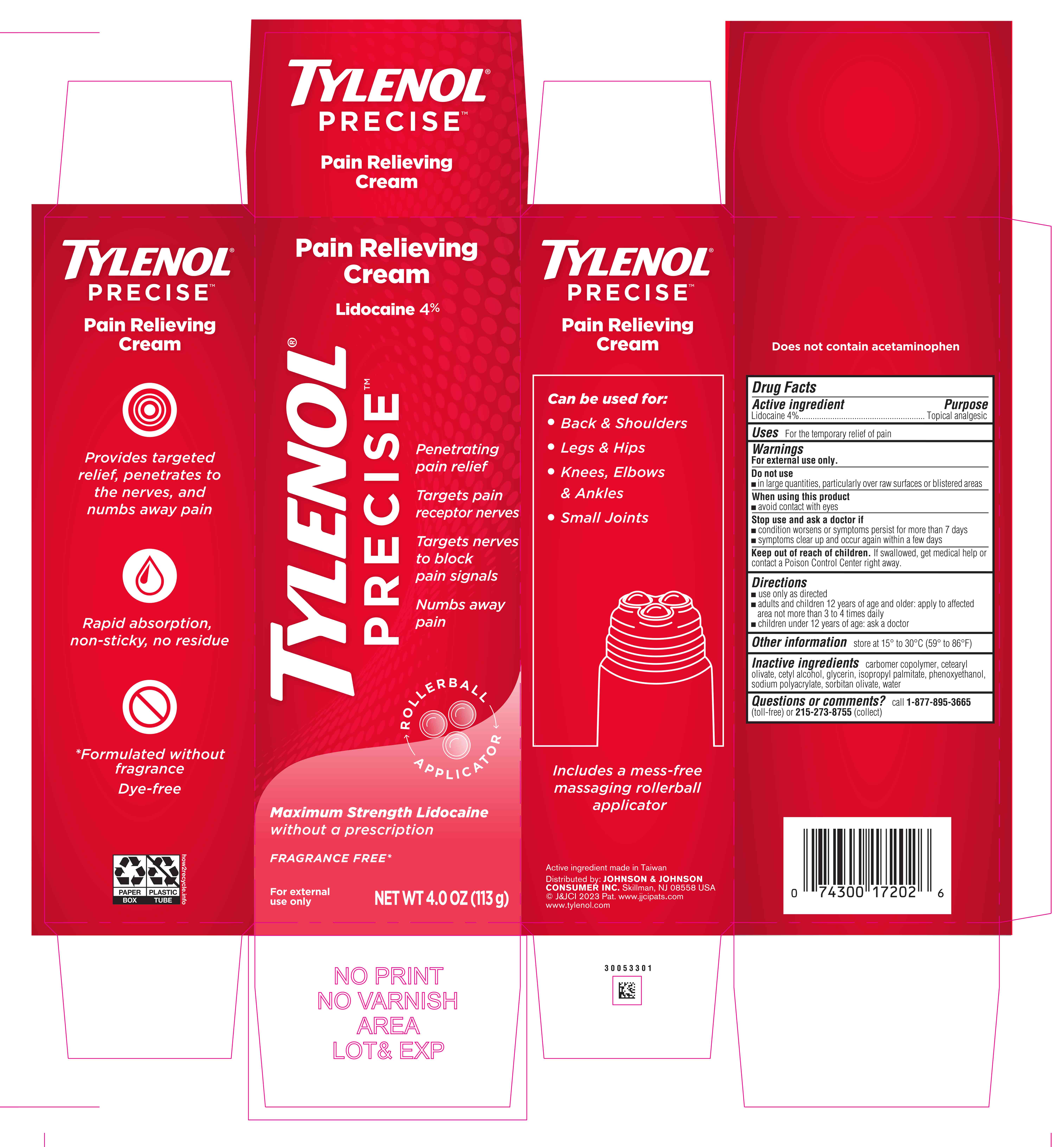 DRUG LABEL: Tylenol Precise Pain Relieving
NDC: 69968-0795 | Form: CREAM
Manufacturer: Kenvue Brands LLC
Category: otc | Type: HUMAN OTC DRUG LABEL
Date: 20241113

ACTIVE INGREDIENTS: LIDOCAINE 40 mg/1 g
INACTIVE INGREDIENTS: WATER; GLYCERIN; PHENOXYETHANOL; SODIUM POLYACRYLATE (2500000 MW); SORBITAN OLIVATE; CETEARYL OLIVATE; CETYL ALCOHOL; ISOPROPYL PALMITATE

Tylenol Precise Pain Relieving Cream

Drug Facts

ACTIVE INGREDIENT

Lidocaine 4% ………………………………………. Topical analgesic

PURPOSE

Topical analgesic

Uses

For the temporary relief of pain

Warnings

- For external use only

Do not use

- in large quantities, particularly over raw surfaces or blistered areas

When using this product

- avoid contact with eyes

Stop use and ask a doctor if

- condition worsens or symptoms persist for more than 7 days
- Symptoms clear up and occur again within a few days

- Keep out of reach of children. If swallowed, get medical help or contact a Poison Control Center right away.

Directions

- use only as directed
- adults and children 12 years of age and older: apply to affected area not more than 3 to 4 times daily
- Children under 12 years of age: ask a doctor

Other Information

- store at 15˚ to 30 ˚C (59 ˚ to 86 ˚F)

Inactive Ingredients

carbomer copolymer, cetearyl olivate, cetyl alcohol, glycerin, isopropyl palmitate, phenoxyethanol, sodium polyacrylate, sorbitan olivate, water

Questions?

call 1-877-895-3665 (toll-free) or 215-273-8755 (collect)

Distributed by:
JOHNSON & JOHNSON CONSUMER INC.
Skillman, NJ 08558 USA

PRINCIPAL DISPLAY PANEL - 113 g Tube Carton

Pain Relieving

Cream

Lidocaine 4%

TYLENOL®

PRECISETM

Penetrating

pain relief

Targets pain

receptor nerves

Targets nerves

to block

pain signals

Numbs away

pain

ROLLER BALL

APPLICATOR

Maximum Strength Lidocaine

without a prescription

FRAGRANCE FREE*

For external

use only

NET WT 4.0 OZ (113 g)